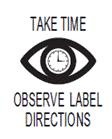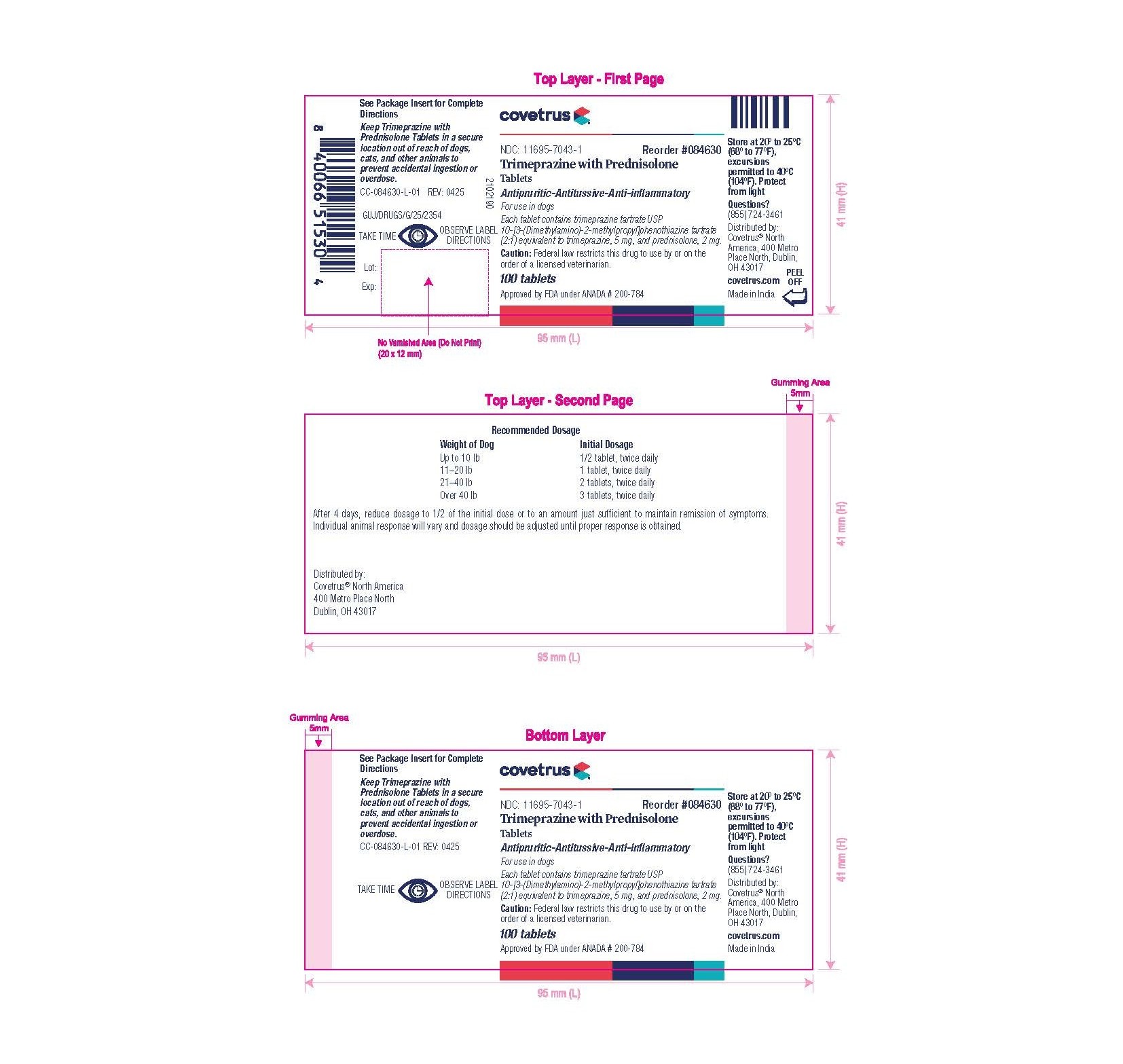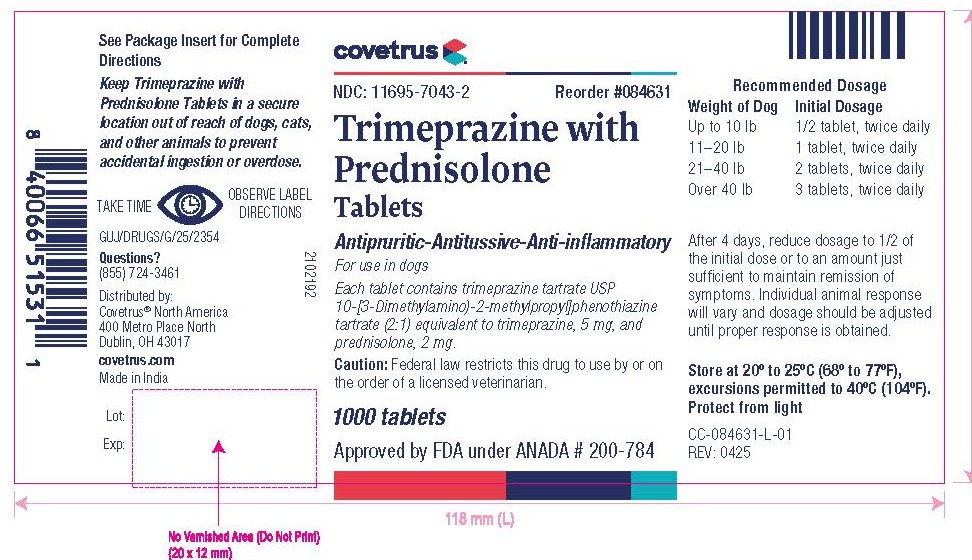 DRUG LABEL: Trimeprazine with Prednisolone
NDC: 11695-7043 | Form: TABLET
Manufacturer: Covetrus North America
Category: animal | Type: PRESCRIPTION ANIMAL DRUG LABEL
Date: 20251014

ACTIVE INGREDIENTS: TRIMEPRAZINE TARTRATE 5 mg/1 1; PREDNISOLONE 2 mg/1 1

Trimeprazine with Prednisolone
Tablets

Antipruritic-Antitussive-Anti-inflammatory

For use in dogs

CAUTION:

Federal law restricts this drug to use by or on the order of a licensed veterinarian.

DESCRIPTION:

Each tablet contains trimeprazine tartrate (USP) 10-[3-(Dimethylamino)-2-methylpropyl]phenothiazine tartrate (2:1) equivalent to trimeprazine, 5 mg, and prednisolone, 2 mg.

Action:

The exclusive Trimeprazine with Prednisolone formula combines the antipruritic and antitussive action of trimeprazine with the anti-inflammatory action of prednisolone. A therapeutic effect is attained by administering the tablets twice daily.

INDICATIONS AND USAGE:

1. Antipruritic: Trimeprazine with Prednisolone is recommended for the relief of itching regardless of cause. Its usefulness has been demonstrated for the relief of itching and the reduction of inflammation commonly associated with most skin disorders of dogs such as the eczema caused by internal disorders, otitis, and dermatitis (allergic, parasitic, pustular, and nonspecific). It often relieves pruritus which does not respond to other therapy. With any pruritus treatment, the cause should be determined and corrected; otherwise, signs are likely to recur following discontinuance of therapy.

2. Antitussive: Trimeprazine with Prednisolone has been found to be effective therapy and adjunctive therapy in various cough conditions of dogs. Therefore, in addition to its anti pruritic action, Trimeprazine with Prednisolone is recommended for the treatment of "kennel cough" or tracheobronchitis, bronchitis including all allergic bronchitis, and infections and coughs of nonspecific origin. (Coughs due to cardiac insufficiencies would not be expected to respond to Trimeprazine with Prednisolone therapy.) As with any antitussive treatment, the etiology of the cough should be determined and eliminated if possible. Otherwise, symptoms are likely to recur following discontinuance of therapy.

Note: Trimeprazine with Prednisolone may be administered to animals suffering from acute or chronic bacterial infections provided the infection is controlled by appropriate antibiotic or chemotherapeutic agents.

WARNINGS:

Clinical and experimental data have demonstrated that corticosteroids administered orally or by injection to animals may induce the first stage of parturition if used during the last trimester of pregnancy and may precipitate premature parturition followed by dystocia, fetal death, retained placenta, and metritis. Additionally, corticosteroids administered to dogs, rabbits, and rodents during pregnancy have resulted in cleft palate in offspring. Corticosteroids administered to dogs during pregnancy have also resulted in other congenital anomalies, including deformed forelegs, phocomelia, and anasarca. If a vasoconstrictor is needed, norepinephrine should be used in lieu of epinephrine. Phenothiazine derivatives may reverse the usual elevating action of epinephrine causing a further lowering of blood pressure.

Keep Trimeprazine with Prednisolone Tablets in a secure location out of reach of dogs, cats, and other animals to prevent accidental ingestion or overdose.

CONTACT INFORMATION:

To report suspected adverse drug experiences, for technical assistance or to obtain a copy of the Safety Data Sheet (SDS), contact Covetrus® North America at (855) 724-3461. For additional information about adverse drug experience reporting for animal drugs, contact FDA at 1-888-FDA-VETS or http://www.fda.gov/reportanimalae

PRECAUTIONS AND SIDE EFFECTS:

All the precautions applicable to cortisone and to phenothiazine derivatives apply also to Trimeprazine with Prednisolone. Possible side effects attributable to corticosteroids include sodium retention and potassium loss, negative nitrogen balance, suppressed adrenal cortical function, delayed wound healing, osteoporosis, elevated levels of SGPT and SAP, and vomiting and diarrhea (occasionally bloody). Cushings syndrome in dogs has been reported in association with prolonged or repeated steroid therapy. Possible increased susceptibility to bacterial invasion and/or the exacerbation of preexisting bacterial infection may occur in patients receiving corticosteroids. As noted above, however, this problem can be avoided by concomitant use of appropriate anti-infective agents. Possible side effects attributable to phenothiazine derivatives include sedation; protruding nictitating membrane; blood dyscrasias; intensification and prolongation of the action of analgesics, sedatives and general anesthetics; and potentiation of organophosphate toxicity and the activity of procaine hydrochloride.

It should be remembered that the premonitory signs of cortisone overdosage, such as sodium retention and edema, may not occur with prednisolone. Therefore, the veterinarians must be alert to detect less obvious side effects, such as blood dyscrasias, polydipsia, and polyuria.

The appearance and severity of side effects are dose related and are minimal at the recommended dosage level. If troublesome side effects are encountered, the dosage of Trimeprazine with Prednisolone should be reduced and discontinued unless the severity of the condition being treated makes its relief paramount.

Prolonged treatment with Trimeprazine with Prednisolone must be withdrawn gradually. Use of corticosteroids, depending on dose, duration, and specific steroid, may result in inhibition of endogenous steroid production following drug withdrawal. In patients presently receiving or recently withdrawn from systemic steroid treatments, therapy with a rapidly acting corticosteroid should be considered in unusually stressful situations.

DOSAGE AND ADMINISTRATION:

The same dosage schedule may be followed for both antipruritic and antitussive therapy.

Weight of Dog | Initial Dosage
Up to 10 lb | 1/2 tablet, twice daily
11–20 lb | 1 tablet, twice daily
21–40 lb | 2 tablets, twice daily
Over 40 lb | 3 tablets, twice daily

After 4 days, reduce dosage to 1/2 of the initial dose or to an amount just sufficient to maintain remission of symptoms. Individual animal response will vary and dosage should be adjusted until proper response is obtained.

Store at 20° to 25°C (68° to 77°F), excursions permitted to 40°C (104°F). Protect from light.

HOW SUPPLIED:

100- and 1000-tablet bottles.

REFERENCES:

1. Knowles JO, Knowles RP: Preliminary reports on an effective antipruritic agent. Vet Med 55(8):67–68, 1960.

2. Candlin FT: An agent to aid in control of pruritus. Vet Med 56(5):207–208, 1961.

3. Yoxall AT, Hird JRF: Pharmacological Basis of Small Animal Medicine. Blackwell Scientific Publications, London, pp. 99–102, 1979.

4. Booth N, McDonald LE: Veterinary Pharmacology and Therapeutics, 5th ed. Iowa State University Press, Ames, pp. 564–570, 1982.

5. Davis L: Handbook of Small Animal Therapeutics. Churchill Livingstone, New York, pp. 140–142; 459–461; 468–469, 1985.

6. Scott D: Systemic glucocorticoid therapy. Current Veterinary Therapy, Kirk WV Saunders, ed., Philadelphia, pp. 988–994, 1980.

7. Lecture: "Rational Steroid Therapy" Duncan C. Ferguson, VMD, PhD, Department of Pharmacology, Cornell University.

8. Kemppianen RJ, Lorenz MD, Thompson FN: Adrenocortical suppression in the dog given a single intramuscular dose of prednisolone or triamcinolone acetonide. Am J Vet Res 42(2):204–206, 1982.

9. Rogers WA, Ruebner BH: A retrospective study of probable glucocorticoid induced hepatopathy in dogs. JAVMA 1977;170(6): 603-605.

Approved by FDA under ANADA # 200-784

Distributed by:

Covetrus® North America

400 Metro Place North

Dublin, OH 43017

© 2025 Covetrus, Inc. All rights reserved.

covetrus.com

REV: 0425

PRINCIPAL DISPLAY PANEL - 100 Tablet Bottle Label

NDC: 11695-7043-1

Trimeprazine with Prednisolone

Tablets

Antipruritic–Antitussive–Anti-inflammatory

For use in dogs

Each tablet contains trimeprazine tartrate USP

10-[3-(Dimethylamino)-2-methylpropyl]phenothiazine

tartrate (2:1) equivalent to trimeprazine, 5 mg, and

prednisolone, 2 mg.

Caution: Federal law restricts this drug to use by or on the order of a licensed veterinarian.

100 tablets

Approved by FDA under ANADA # 200-784

PRINCIPAL DISPLAY PANEL - 1000 Tablet Bottle Label

NDC: 11695-7043-2

Trimeprazine with Prednisolone

Tablets

Antipruritic–Antitussive–Anti-inflammatory

For use in dogs

Each tablet contains trimeprazine tartrate USP

10-[3-(Dimethylamino)-2-methylpropyl]phenothiazine

tartrate (2:1) equivalent to trimeprazine, 5 mg, and

prednisolone, 2 mg.

Caution: Federal law restricts this drug to use by or on the order of a licensed veterinarian.

1000 tablets

Approved by FDA under ANADA # 200-784